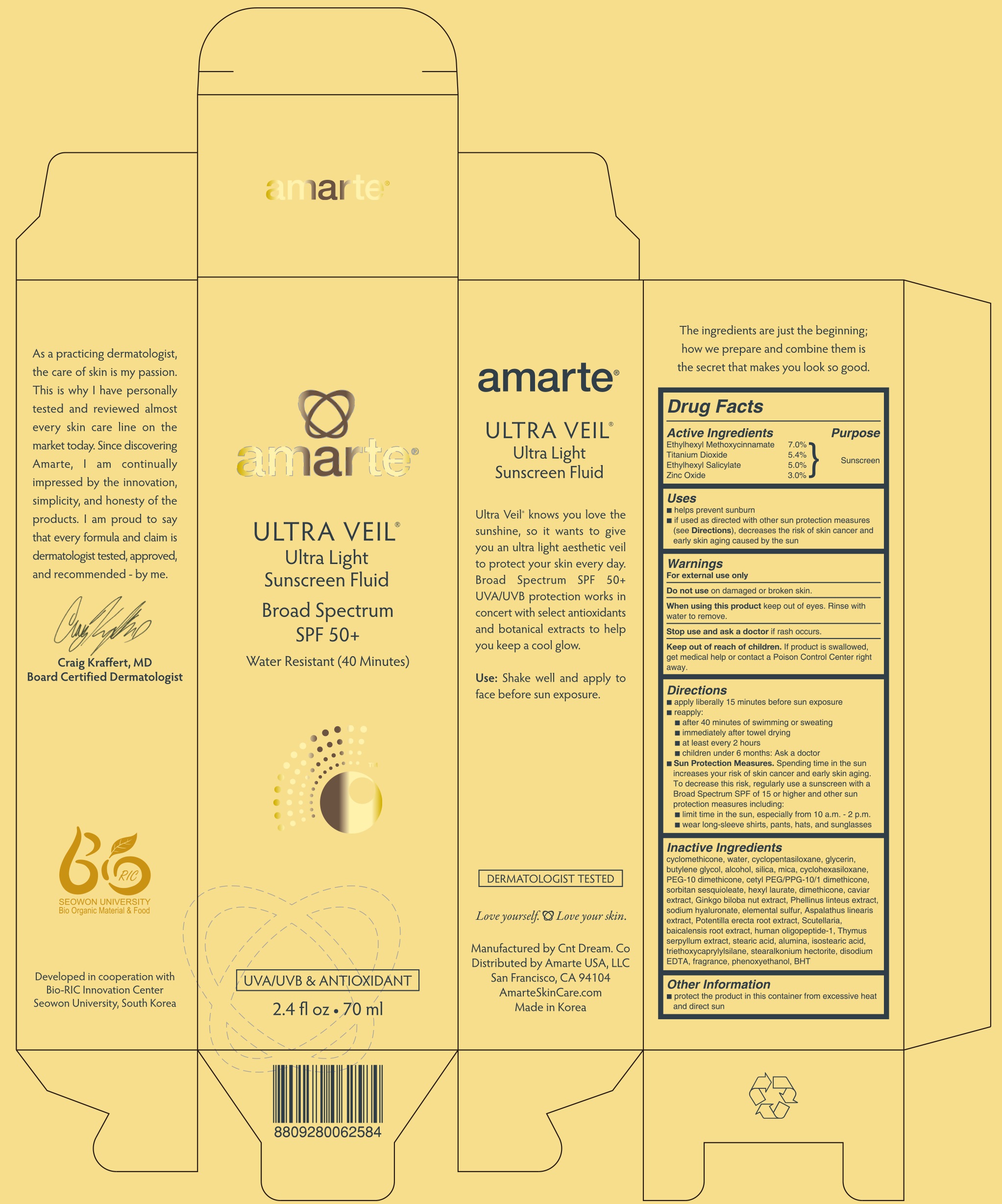 DRUG LABEL: AMARTE ULTRA VEIL ULTRA LIGHT SUNSCREEN FLUID
NDC: 69352-020 | Form: CREAM
Manufacturer: AMARTEINTERNATIONAL CO., LTD.
Category: otc | Type: HUMAN OTC DRUG LABEL
Date: 20240731

ACTIVE INGREDIENTS: OCTINOXATE 4.9 mg/70 mL; TITANIUM DIOXIDE 3.78 mg/70 mL; OCTISALATE 3.5 mg/70 mL; ZINC OXIDE 2.1 mg/70 mL
INACTIVE INGREDIENTS: WATER

ACTIVE INGREDIENT

Active Ingredients: Ethylhexyl Methoxycinnamate 7.0%, Titanium Dioxide 5.4%, Ethylhexyl Salicylate 5.0%, Zinc Oxide 3.0%

INACTIVE INGREDIENT

Inactive Ingredients:
cyclomethicone, water, cyclopentasiloxane, glycerin, butylene glycol, alcohol, silica, mica, cyclohexasiloxane, PEG-10 dimethicone, cetyl PEG/PPG-10/1 dimethicone, sorbitan sesquioleate, hexyl laurate, dimethicone, caviar extract, Ginkgo biloba nut extract, Phellinus linteus extract, sodium hyaluronate, elemental sulfur, Aspalathus linearis extract, Potentilla erecta root extract, Scutellaria, baicalensis root extract, human oligopeptide-1, Thymus serpyllum extract, stearic acid, alumina, isostearic acid, triethoxycaprylylsilane, stearalkonium hectorite, disodium EDTA, fragrance, phenoxyethanol, BHT

PURPOSE

PURPOSE: SUNSCREEN

WARNINGS

For external use only
Do not use on damaged or broken skin.
When using this product keep out of eyes. Rinse with water to remove.
Stop use and ask a doctor if rash occurs.
Keep out of reach of children. If product is swallowed, get medical help or contact a Poison Control Center right away.

Keep out of reach of children. If product is swallowed, get medical help or contact a Poison Control Center right away.

Uses

- helps prevent sunburn
- if used as directed with other sun protection measures (see Directions), decreases the risk of skin cancer and early skin aging caused by the sun

Directions

- apply liberally 15 minutes before sun exposure
- reapply:
- after 40 minutes of swimming or sweating
- immediately after towel drying
- at least every 2 hours
- children under 6 months: Ask a doctor
- Sun Protection Measures. Spending time in the sun increases your risk of skin cancer and early skin aging. To decrease this risk, regularly use a sunscreen with a Broad Spectrum SPF of 15 or higher and other sun protection measures including:
limit time in the sun, especially from 10 a.m. - 2 p.m.
wear long-sleeve shirts, pants, hats, and sunglasses